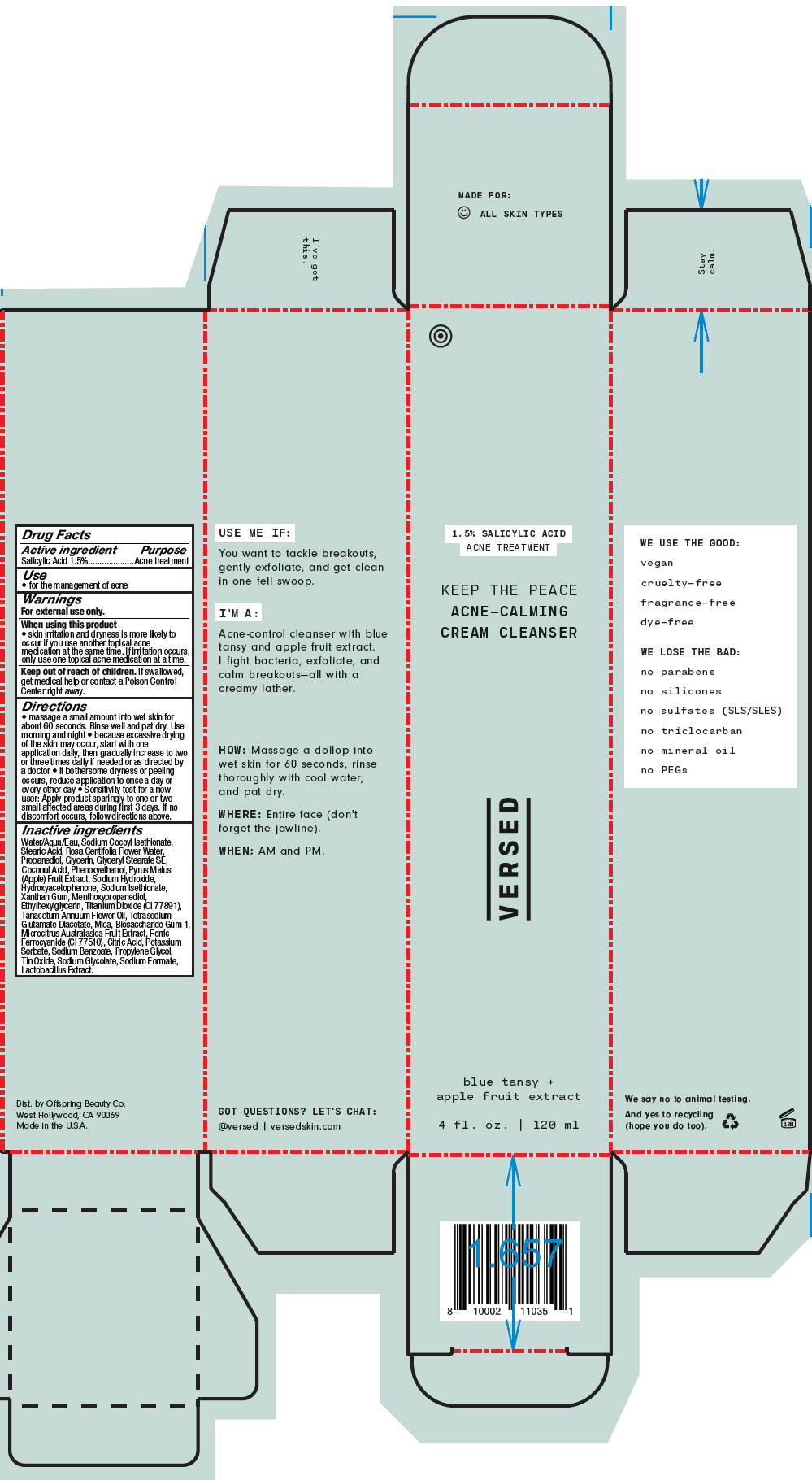 DRUG LABEL: Keep the Peace Acne-Calming Cream Cleanser
NDC: 73690-024 | Form: RINSE
Manufacturer: Offspring Beauty Co. / Versed
Category: otc | Type: HUMAN OTC DRUG LABEL
Date: 20240109

ACTIVE INGREDIENTS: Salicylic Acid 15 mg/1 mL
INACTIVE INGREDIENTS: WATER; SODIUM COCOYL ISETHIONATE; STEARIC ACID; ROSA CENTIFOLIA FLOWER OIL; PROPANEDIOL; GLYCERIN; GLYCERYL STEARATE SE; PHENOXYETHANOL; APPLE; SODIUM HYDROXIDE; HYDROXYACETOPHENONE; XANTHAN GUM; 3-((L-MENTHYL)OXY)PROPANE-1,2-DIOL; ETHYLHEXYLGLYCERIN; TANACETUM ANNUUM FLOWERING TOP OIL; TETRASODIUM GLUTAMATE DIACETATE; BIOSACCHARIDE GUM-1; MICROCITRUS AUSTRALIS FRUIT; PROPYLENE GLYCOL; LACTOBACILLUS BREVIS; TITANIUM DIOXIDE; MICA; FERRIC FERROCYANIDE; COCONUT ACID; SODIUM ISETHIONATE; CITRIC ACID MONOHYDRATE; POTASSIUM SORBATE; SODIUM BENZOATE; STANNIC OXIDE; SODIUM GLYCOLATE; SODIUM FORMATE

Keep the Peace Acne-Calming Cream Cleanser

Drug Facts

Active ingredient

Salicylic Acid 1.5%

Purpose

Acne treatment

Use

- for the management of acne

Warnings

For external use only.

When using this product

- skin irritation and dryness is more likely to occur if you use another topical acne medication at the same time. If irritation occurs, only use one topical acne medication at a time.

Keep out of reach of children. If swallowed, get medical help or contact a Poison Control Center right away.

Directions

- massage a small amount into wet skin for about 60 seconds. Rinse well and pat dry. Use morning and night
- because excessive drying of the skin may occur, start with one application daily, then gradually increase to two or three times daily if needed or as directed by a doctor
- if bothersome dryness or peeling occurs, reduce application to once a day or every other day
- Sensitivity test for a new user: Apply product sparingly to one or two small affected areas during first 3 days. If no discomfort occurs, follow directions above.

Inactive ingredients

Water/Aqua/Eau, Sodium Cocoyl Isethionate, Stearic Acid, Rosa Centifolia Flower Water, Propanediol, Glycerin, Glyceryl Stearate SE, Coconut Acid, Phenoxyethanol, Pyrus Malus (Apple) Fruit Extract, Sodium Hydroxide, Hydroxyacetophenone, Sodium Isethionate, Xanthan Gum, Menthoxypropanediol, Ethylhexylglycerin, Titanium Dioxide (CI 77891), Tanacetum Annuum Flower Oil, Tetrasodium Glutamate Diacetate, Mica, Biosaccharide Gum-1, Microcitrus Australasica Fruit Extract, Ferric Ferrocyanide (CI 77510), Citric Acid, Potassium Sorbate, Sodium Benzoate, Propylene Glycol, Tin Oxide, Sodium Glycolate, Sodium Formate, Lactobacillus Extract.

Dist. by Offspring Beauty Co.
West Hollywood, CA 90069

PRINCIPAL DISPLAY PANEL - 120 ml Tube Carton

1.5% SALICYLIC ACID
ACNE TREATMENT

KEEP THE PEACE
ACNE-CALMING
CREAM CLEANSER

VERSED

blue tansy +
apple fruit extract

4 fl. oz. | 120 ml